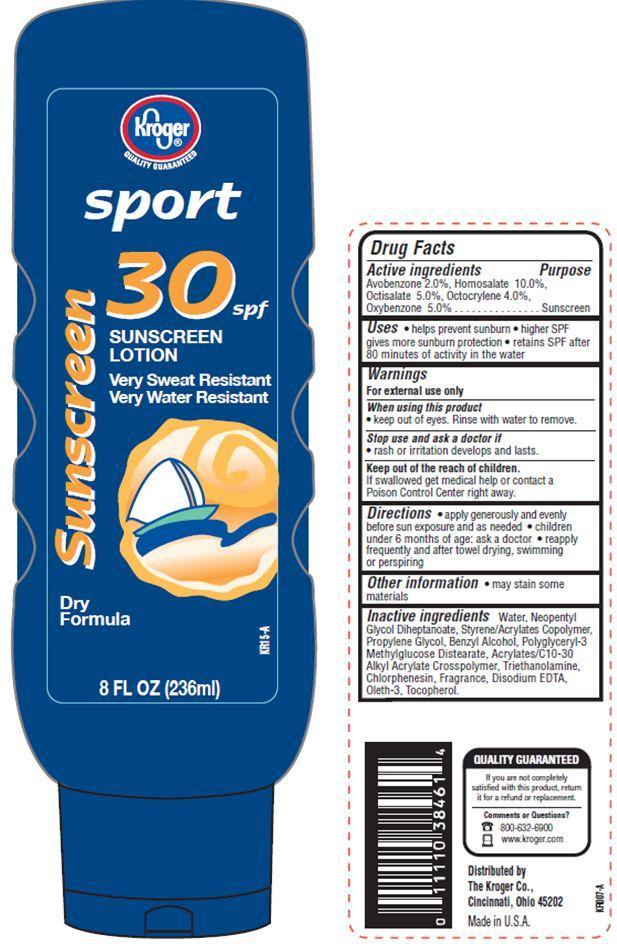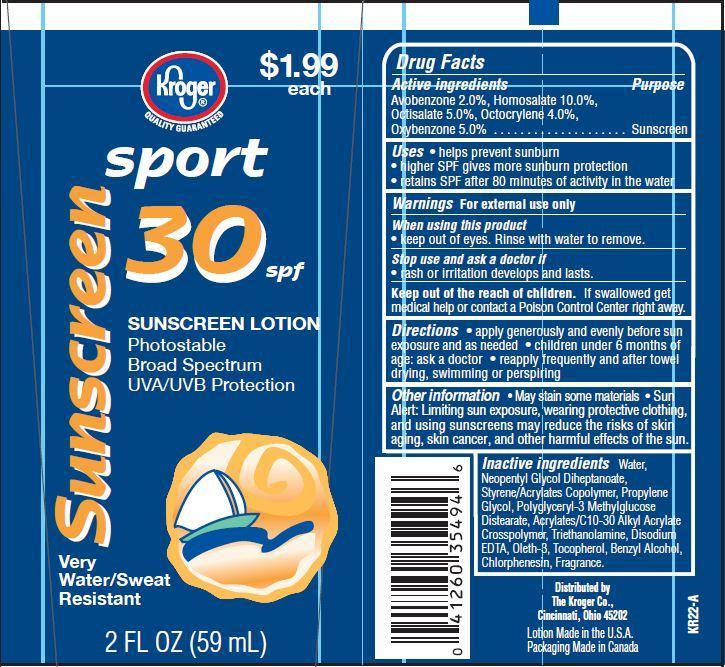 DRUG LABEL: Kroger Sport Sunscreen 
NDC: 30142-901 | Form: LOTION
Manufacturer: THE KROGER CO
Category: otc | Type: HUMAN OTC DRUG LABEL
Date: 20121119

ACTIVE INGREDIENTS: AVOBENZONE 2 g/100 g; HOMOSALATE 10 g/100 g; OCTISALATE 5 g/100 g; OCTOCRYLENE 4 g/100 g; OXYBENZONE 5 g/100 g
INACTIVE INGREDIENTS: WATER; NEOPENTYL GLYCOL DIHEPTANOATE; PROPYLENE GLYCOL; TROLAMINE; CHLORPHENESIN; BENZYL ALCOHOL; OLETH-3; TOCOPHEROL; EDETATE DISODIUM

Drug Facts

Active ingredients

Avobenzone 2.0 %

Homosalate 10.0%

Octisalate 5.0%

Octocrylene 4.0%

Oxybenzone 5.0%

Purpose

Sunscreen

Uses

- helps prevent sunburn
- higher SPF gives more sunburn protection
- retains SPF after 80 minutes of activity in the water

Warnings

For external use only

When using this product

- keep out of eyes. Rinse with water to remove.

Stop use and ask a doctor if

- rash or irritation develops and lasts

Keep out of reach of children.

If swallowed get medical help or contact a Poison Control Center right away.

Other information

- May stain some materials
- Sun Alert: Limiting sun exposure, wearing protective clothing, and using sunscreens may reduce the risks of skin aging, skin cancer, and other harmful effects of the sun.

Directions

- apply generously and evenly before sun exposure and as needed
- children under 6 months of age:ask a doctor
- reapply frequently and after towel drying, swimming or perspiring.

Inactive ingredients

Water, Neopentyl Glycol Diheptanoate, Styrene/Acrylates Copolymer, Propylene Glycol, Polyglyceryl-3 Methylglucose Distearate, Benzyl Alcohol, Acrylates/C10-30 Alkyl Acrylate Crosspolymer, Triethanolamine, Disodium EDTA, Oleth-3, Tocopherol, Chlorphenesin, Fragrance.

Principal Display Panel

Kroger
QUALITY GUARANTEED
sport
30 spf
SUNSCREEN
LOTION
Very Sweat Resistant
Very Water Resistant
Dry Formula
8 FL OZ (236ml)
kroger
sport
30 spf
SUNSCREEN LOTION
Photostable
Broad Spectrum
UVA/UVB Protection
Very
Water/ Sweat
Resistant
2 FL OZ (59 mL)